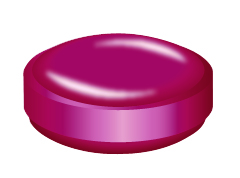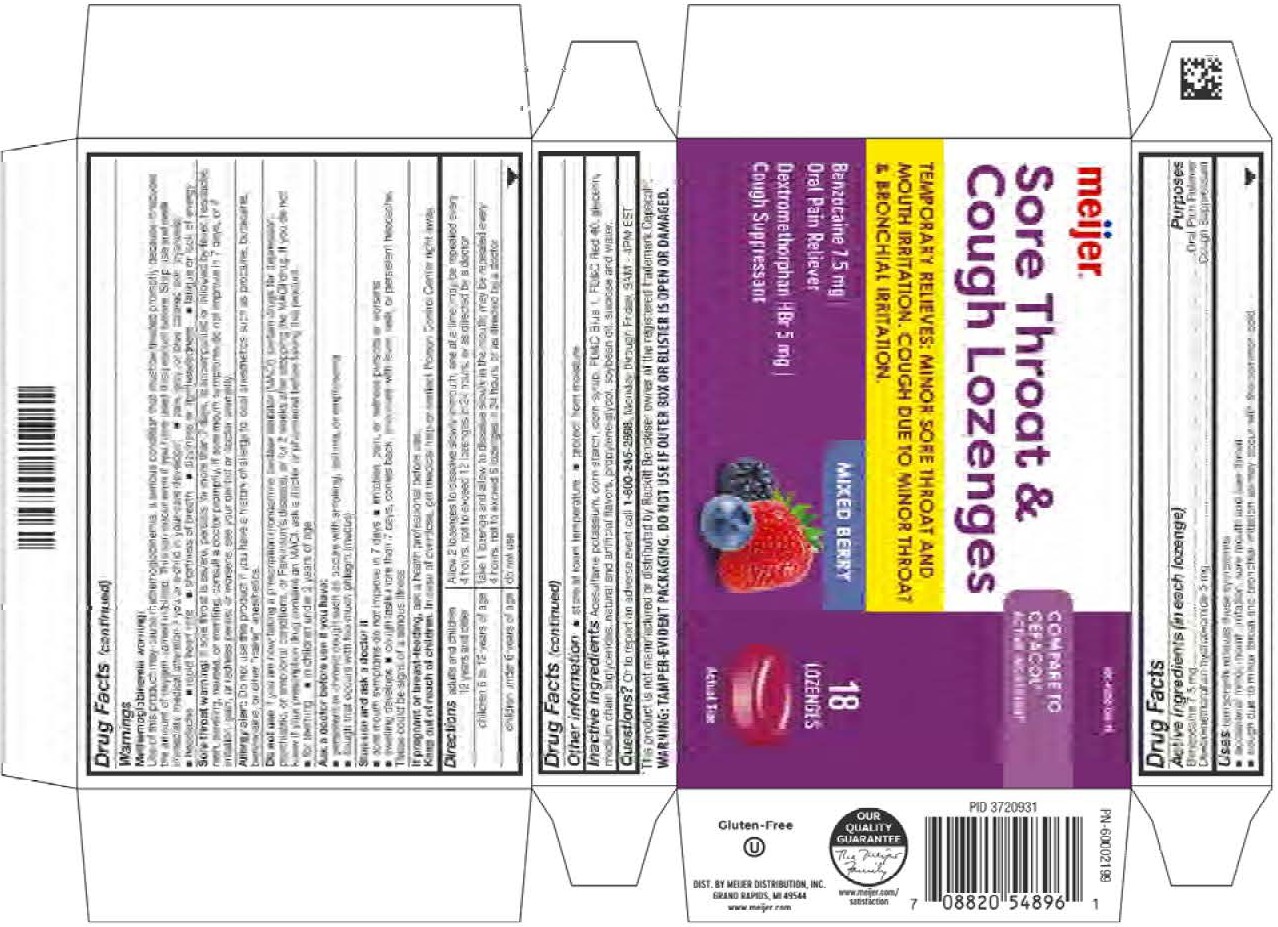 DRUG LABEL: Mixed Berry Sore Throat and  Cough lozenge
NDC: 41250-066 | Form: LOZENGE
Manufacturer: Meijer Distribution, Inc.
Category: otc | Type: HUMAN OTC DRUG LABEL
Date: 20260202

ACTIVE INGREDIENTS: BENZOCAINE 7.5 mg/1 1; DEXTROMETHORPHAN HYDROBROMIDE 5 mg/1 1
INACTIVE INGREDIENTS: WATER

Benzocaine 7.5mg
Dextromethorphan Hydrobromide 5mg

Active ingredients (in each lozenge)

Benzocaine 7.5 mg

Dextromethorphan hydrobromide 5 mg

Purpose

Oral Pain Reliever

Cough Suppressant

INDICATIONS AND USAGE

Uses temporarily relieves these symptoms:

occasional minor mouth irritation, sore mouth and sore throat

cough due to minor throat and bronchial irritationas may occur with a common cold

Warnings

Methemoglobinemia warning:

Use of this product may cause methemoglobinemia, a serious condition that must be treated promptly because it reduces the amount of oxygen carried in blood. This can occur even if you have used this product before. Stop use and seek immediate medical attention if you or a child in your care develops:

- pale, gray, or blue colored skin (cyanosis)
- headache
- rapid heart rate
- shortness of breath
- dizziness or lightheadedness
- fatigue or lack of energy

Sore throat warning: If sore throat is severe, persists for more than 2 days, is accompanied or followed by fever, headache, rash, swelling, nausea or vomiting, consult a doctor promptly. If sore mouth symptoms do not improve in 7 days, or if irritation, pain, or redness persists or worsens, see your dentist or doctor promptly.

Allergy alert: Do not use this product if you have a history of allergy to local anesthetics such as procaine, butacaine, benzocaine, or other "caine" anesthetics.

Do not use if you are now taking a presciption monoamine oxidase inhibitor (MAOI) (certain drugs for depression, psychiatric, or emotional conditions, or Parkinson's disease), or for 2 weeks after stopping the MAOI drug. If you do not know if your prescription drug contains an MAOI, ask a doctor or pharmacist before taking this product.

- for teeting
- in children under 2 years of age

Ask a doctor before use if you have:

- persistent or chronic cough such as occurs with smoking, asthma, or emphysema
- cough that occurs with too much phlegm (mucus)

Stop use and ask a doctor if

- sore mouth symptoms do not improve in 7 days
- irritation, pain, or redness persists or worsens
- swelling develops
- cough lasts more than 7 days, comes back, or occurs with feaver, rash, or persistent headache. These could be signs of a serious illness

PREGNANCY OR BREAST FEEDING

If pregnant or breast-feeding, ask a health professional before use.

Keep out of reach of children.

OVERDOSAGE

In case of overdose, get medical help or contact Poison Control Center right away.

Directions

adults and children 12 years and older: Allow 2 lozenages to dissolve slowly in mouth, one at a time. May be repeated every 4 hours, not to exceed 12 lozenges in 24 hours, or as directed by a doctor

children 6 to 12 years of age: take1 lozenge and allow to dissolve slowly in the mouth. May be repeated every 4 hours, not to exceed 6 lozenges in 24 hours, or as directed by a doctor

children under 6 years of age: do not use

Other information

- store at room temperature
- protect from moisture

INACTIVE INGREDIENT

Inactive ingredients: Acesulfame potassium, corn starch, corn syrup, FD&C blue 1, FD&C red 40, glycerin, medium chain triglycerides, natural and artificial flavors, propylene glycol, soybean oil, sucrose and water.

QUESTIONS

Questions? or to report an adverse event call 1-800-245-2898, Monday through Friday, 9AM - 4PM EST